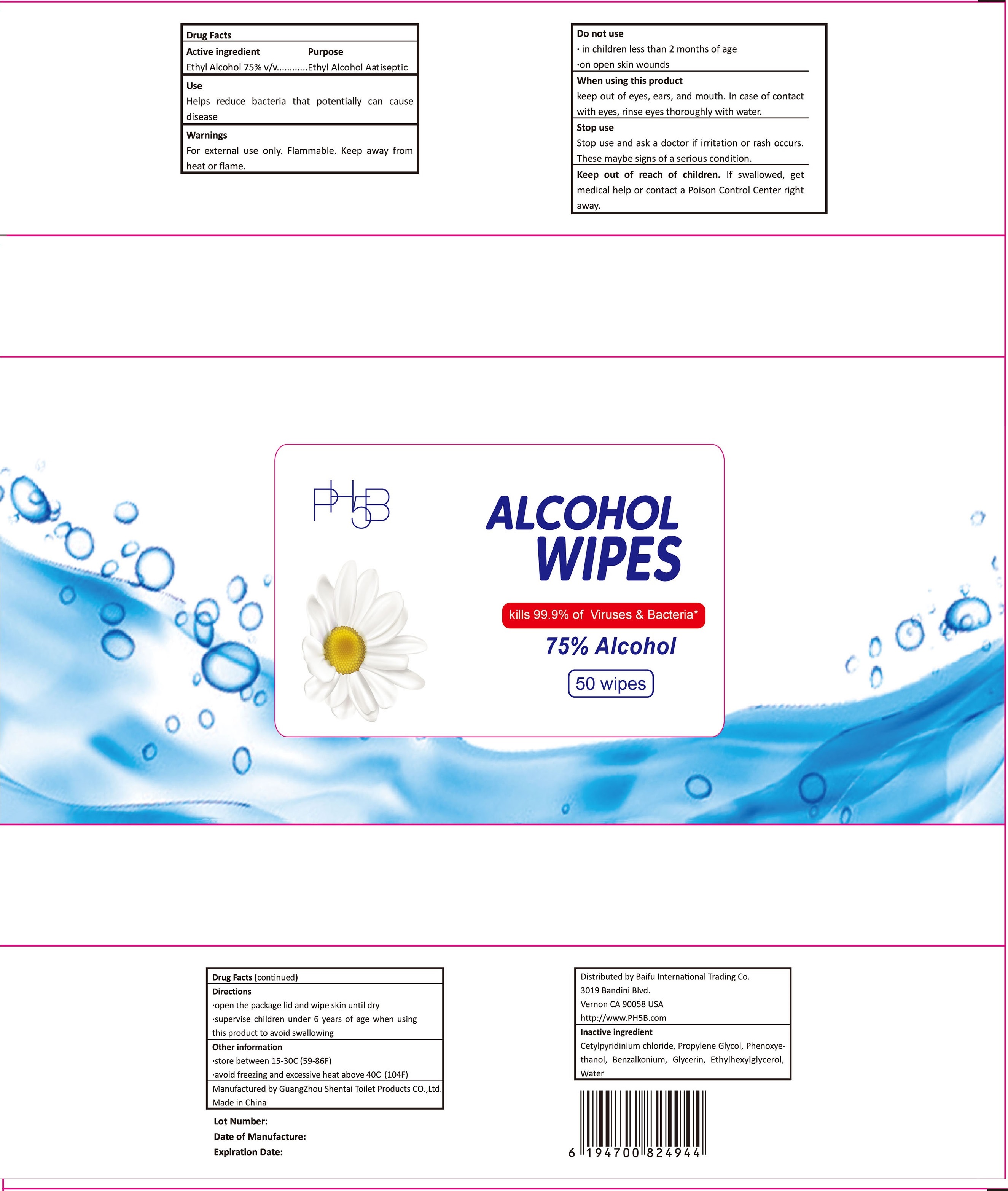 DRUG LABEL: PH5B Alcohol Wipes
NDC: 77119-455 | Form: SOLUTION
Manufacturer: Guangzhou Shentai Hygienic Products Co., Ltd
Category: otc | Type: HUMAN OTC DRUG LABEL
Date: 20200515

ACTIVE INGREDIENTS: ALCOHOL 75 mL/100 mL
INACTIVE INGREDIENTS: CETYLPYRIDINIUM CHLORIDE; PROPYLENE GLYCOL; PHENOXYETHANOL; BENZALKONIUM; GLYCERIN; ETHYLHEXYLGLYCERIN; WATER

Guangzhou Shentai Hygienic Products Co., Ltd

Active Ingredient

Ethyl Alcohol 75% v/v

Purpose

Ethyl Alcohol Antiseptic

Use

Helps reduce bacteria that potentially can cause disease.

Warnings

For external use only. Flammable. Keep away from heat or flame.

Do not use

- in children less than 2 months of age.
- on open skin wounds.

When using this product

keep out of eyes, ears, and mouth. In case of contact with eyes, rinse eyes thoroughly with water.

Stop use

Stop use and ask a doctor if irritation or rash occurs. These may be signs of a serious condition.

Keep out of reach of children.

If swallowed, get medical help or contact a Poison Control Center right away.

Directions

- Open the package lid and wipe skin until dry.
- Supervise children under 6 years of age when using this product to avoid swallowing.

Other information

- Store between 15-30C (59-86F)
- Avoid freezing and excessive heat above 40C (104F)

Manufactured by Guangzhou Shentai Hygienic Products Co.,Ltd
Guangzhou, Guangdong, China
Made in China

Distributed by Baifu International Trading Co.
3019 Bandini Blvd, Vernon, CA 90023
Phone: (323)269-2986
Email: baifumicahel@yahoo.com

Inactive ingredients

CETYLPYRIDINIUM CHLORIDE, PROPYLENE GLYCOL, PHENOXYETHANOL, BENZALKONIUM, GLYCERIN, ETHYLHEXYLGLYCERIN, WATER

Package Label - Principal Display Panel

NDC Number: 77119-445-50